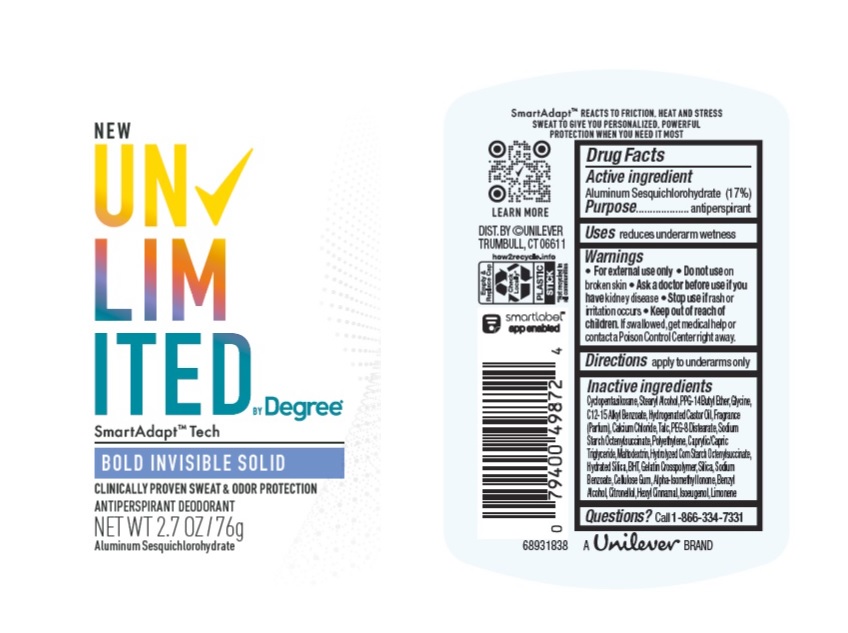 DRUG LABEL: Unlimited by Degree
NDC: 64942-2010 | Form: STICK
Manufacturer: Conopco Inc. d/b/a/ Unilever
Category: otc | Type: HUMAN OTC DRUG LABEL
Date: 20241106

ACTIVE INGREDIENTS: ALUMINUM SESQUICHLOROHYDRATE 17 g/100 g
INACTIVE INGREDIENTS: BENZYL ALCOHOL; .ALPHA.-HEXYLCINNAMALDEHYDE; ISOMETHYL-.ALPHA.-IONONE; .BETA.-CITRONELLOL, (R)-; LIMONENE, (+)-; HYDROGENATED CASTOR OIL; ISOEUGENOL; HYDRATED SILICA; SODIUM BENZOATE; GLYCINE; ALKYL (C12-15) BENZOATE; CALCIUM CHLORIDE; CYCLOMETHICONE 5; PPG-14 BUTYL ETHER; MALTODEXTRIN; STEARYL ALCOHOL; BUTYLATED HYDROXYTOLUENE; SILICON DIOXIDE; PEG-8 DISTEARATE; TALC; CARBOXYMETHYLCELLULOSE SODIUM, UNSPECIFIED FORM; HIGH DENSITY POLYETHYLENE; MEDIUM-CHAIN TRIGLYCERIDES

Unlimited by Degree Bold Invisible Solid Antiperspirant Deodorant

Drug Facts

Active ingredient

Aluminum Sesquichlorohydrate (17%)

Purpose

antiperspirant

Uses

reduces underarm wetness

Warnings

• For external use only.
• Do not use on broken skin .
• Ask a doctor before use if you have kidney disease.
• Stop use if rash or irritation occurs.

• Keep out of reach of children.

If swallowed, get medical help or contact a Poison Control Center right away.

Directions

apply to underarms only

Inactive ingredients

Cyclopentasiloxane, Stearyl Alcohol, PPG-14 Butyl Ether, Glycine, C12-15 Alkyl Benzoate, Hydrogenated Castor Oil, Fragrance (Parfum), Calcium Chloride, Talc, PEG-8 Distearate, Sodium Starch Octenylsuccinate, Polyethylene, Caprylic/Capric Triglyceride,, Maltodextrin, Hydrolyzed Corn Starch Octenylsuccinate, Hydrated Silica, BHT, Gelatin Crosspolymer, Silica, Sodium Benzoate, Cellulose Gum, Alpha-Isomethyl Ionone, Benzyl Alcohol, Citronellol, Hexyl Cinnamal, Isoeugenol, Limonene

Questions?

Call toll-free 1-866-334-7331